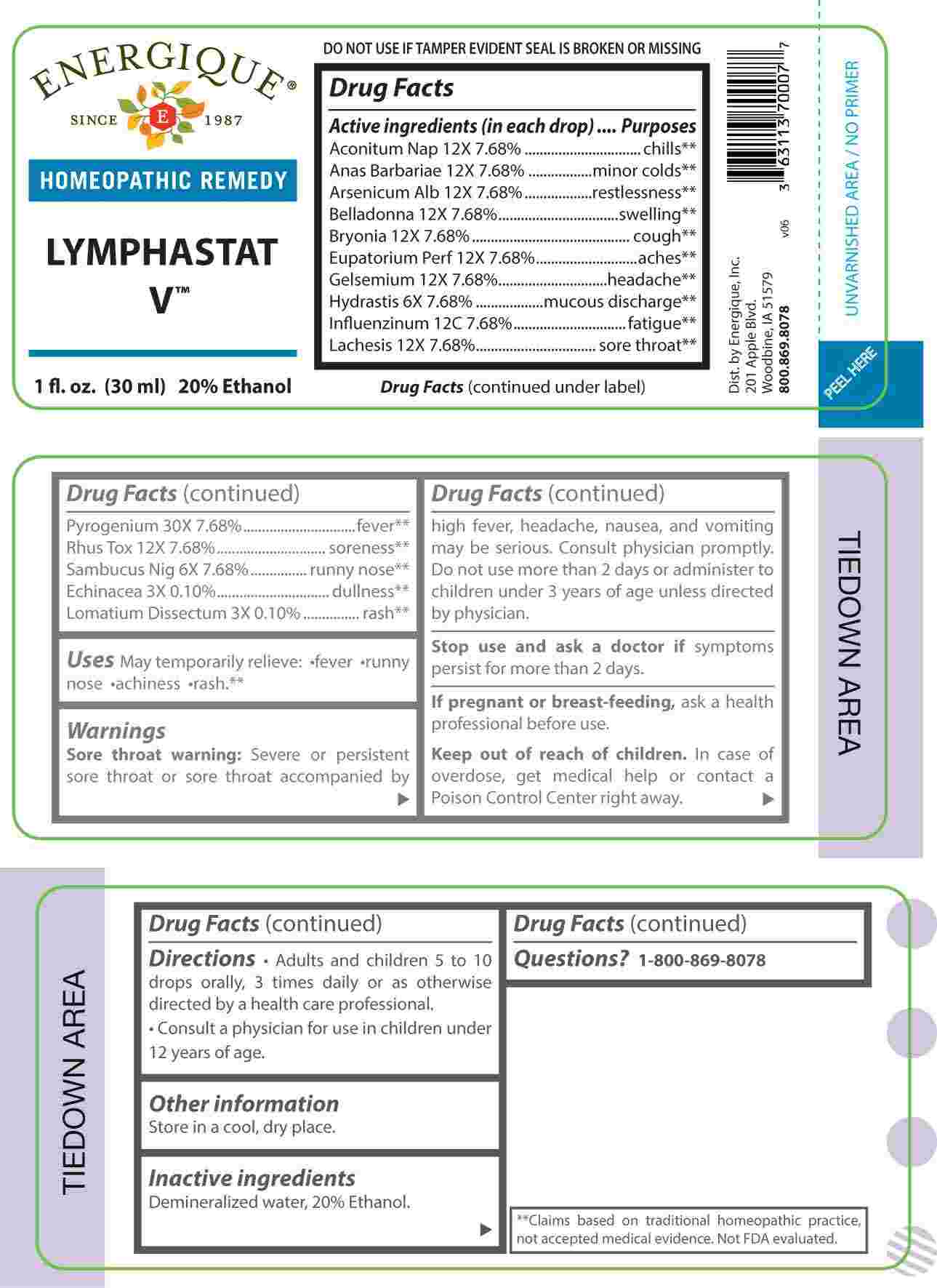 DRUG LABEL: Lymphastat
NDC: 44911-0732 | Form: LIQUID
Manufacturer: Energique, Inc.
Category: homeopathic | Type: HUMAN OTC DRUG LABEL
Date: 20250311

ACTIVE INGREDIENTS: ECHINACEA ANGUSTIFOLIA WHOLE 3 [hp_X]/1 mL; LOMATIUM DISSECTUM ROOT 3 [hp_X]/1 mL; GOLDENSEAL 6 [hp_X]/1 mL; SAMBUCUS NIGRA FLOWERING TOP 6 [hp_X]/1 mL; ACONITUM NAPELLUS WHOLE 12 [hp_X]/1 mL; CAIRINA MOSCHATA HEART/LIVER AUTOLYSATE 12 [hp_X]/1 mL; ARSENIC TRIOXIDE 12 [hp_X]/1 mL; ATROPA BELLADONNA 12 [hp_X]/1 mL; BRYONIA ALBA ROOT 12 [hp_X]/1 mL; EUPATORIUM PERFOLIATUM FLOWERING TOP 12 [hp_X]/1 mL; GELSEMIUM SEMPERVIRENS ROOT 12 [hp_X]/1 mL; LACHESIS MUTA VENOM 12 [hp_X]/1 mL; TOXICODENDRON PUBESCENS LEAF 12 [hp_X]/1 mL; RANCID BEEF 30 [hp_X]/1 mL; INFLUENZA A VIRUS WHOLE 12 [hp_C]/1 mL; INFLUENZA A VIRUS A/DARWIN/6/2021 (H3N2) WHOLE 12 [hp_C]/1 mL; INFLUENZA B VIRUS B/AUSTRIA/1359417/2021 BVR-26 WHOLE 12 [hp_C]/1 mL; INFLUENZA B VIRUS B/PHUKET/3073/2013 BVR-1B WHOLE 12 [hp_C]/1 mL
INACTIVE INGREDIENTS: WATER; ALCOHOL

DRUG FACTS:

ACTIVE INGREDIENTS:

(in each drop) Aconitum Napellus 12X 7.68%, Anas Barbariae 12X 7.68%, Arsenicum Album 12X 7.68%, Belladonna 12X 7.68%, Bryonia 12X 7.68%, Eupatorium Perfoliatum 12X 7.68%, Gelsemium Sempervirens 12X 7.68%, Hydrastis Canadensis 6X 7.68%, Influenzinum 12C 7.68%, Lachesis Mutus 12X 7.68%, Pyrogenium 30X 7.68%, Rhus Tox 12X 7.68%, Sambucus Nigra 6X 7.68%, Echinacea 3X 0.10%, Lomatium Dissectum 3X 0.10%.

PURPOSE:

Aconitum Napellus - chills,** Anas Barbariae – minor colds,** Arsenicum Album - restlessness,** Belladonna - swelling,** Bryonia - cough,** Eupatorium Perfoliatum - aches,** Gelsemium Sempervirens - headache,** Hydrastis Canadensis – mucous discharge,** Influenzinum - fatigue,** Lachesis Mutus – sore throat,** Pyrogenium - fever,** Rhus Tox - soreness,** Sambucus Nigra – runny nose,** Echinacea - dullness,** Lomatium Dissectum – rash.**

**Claims based on traditional homeopathic practice, not accepted medical evidence. Not FDA evaluated.

USES:

May temporary relieve: •fever •runny nose •achiness rash.**

**Claims based on traditional homeopathic practice. Not FDA evaluated.

WARNINGS:

Sore throat warning: Severe or persistent sore throat or sore throat accompanied by high fever, headache, nausea, and vomiting may be serious. Consult physician promptly. Do not use more than 2 days or administer to children under 3 years of age unless directed by physician.

Stop use and ask a doctor if symptoms persist for more than 2 days.

If pregnant or breast-feeding, ask a health professional before use.

Keep out of reach of children. In case of overdose, get medical help or contact a Poison Control Center right away.

Store in a cool, dry place.

DO NOT USE IF TAMPER EVIDENT SEAL IS BROKEN OR MISSING

KEEP OUT OF REACH OF CHILDREN:

In case of overdose, get medical help or contact a Poison Control Center right away.

DIRECTIONS:

• Adults and children 5 to 10 drops orally, 3 times daily or as otherwise directed by a health care professional.

Consult a physician for use in children under 12 years of age.

INACTIVE INGREDIENTS:

Demineralized water, 20% Ethanol.

QUESTIONS:

Dist. by Energique, Inc.

201 Apple Blvd.

Woodbine, IA 51579

800-869-8078

PACKAGE LABEL DISPLAY:

ENERGIQUE

SINCE 1987

HOMEOPATHIC REMEDY

LYMPHASTAT V

1 fl. oz. (30 ml)